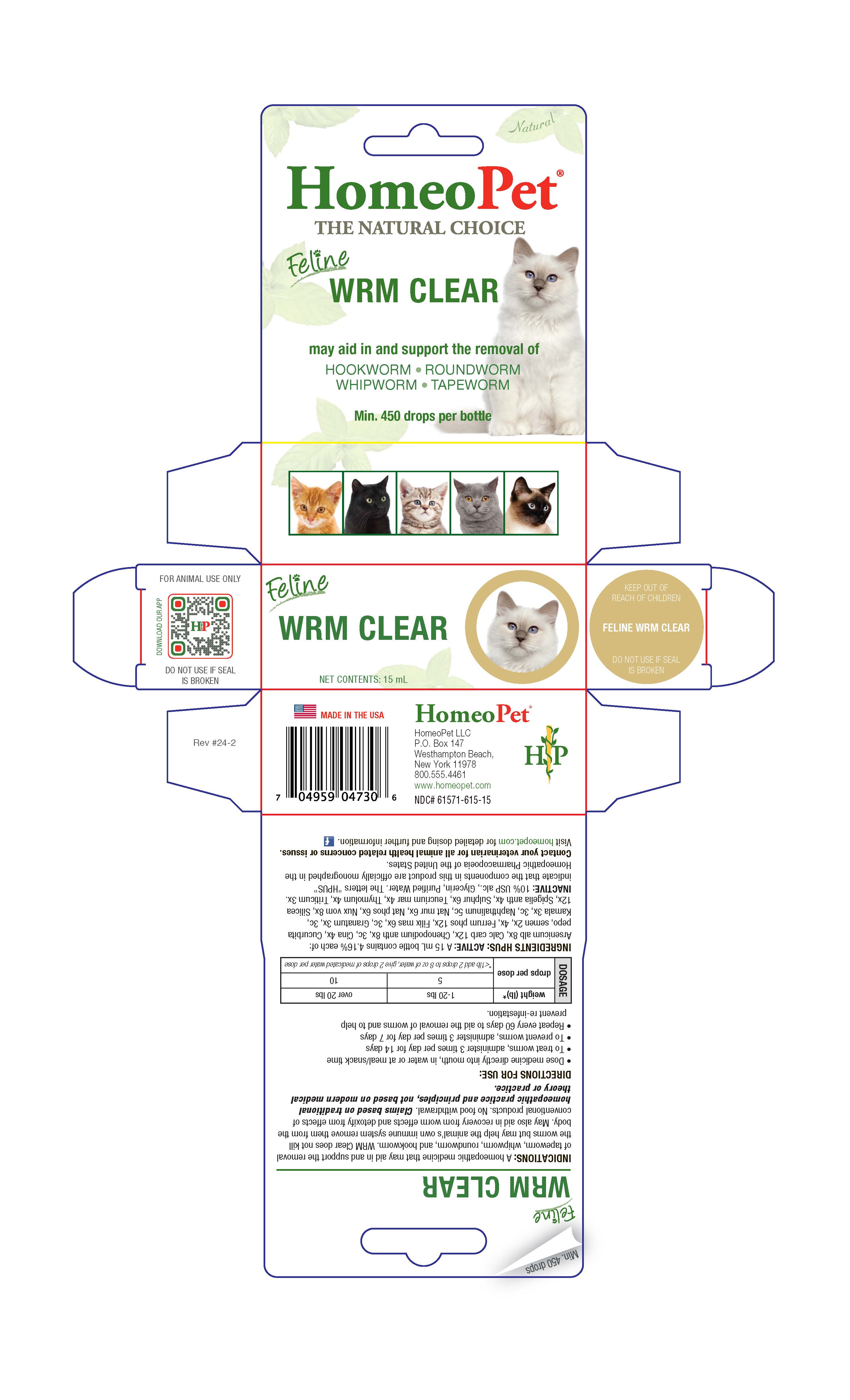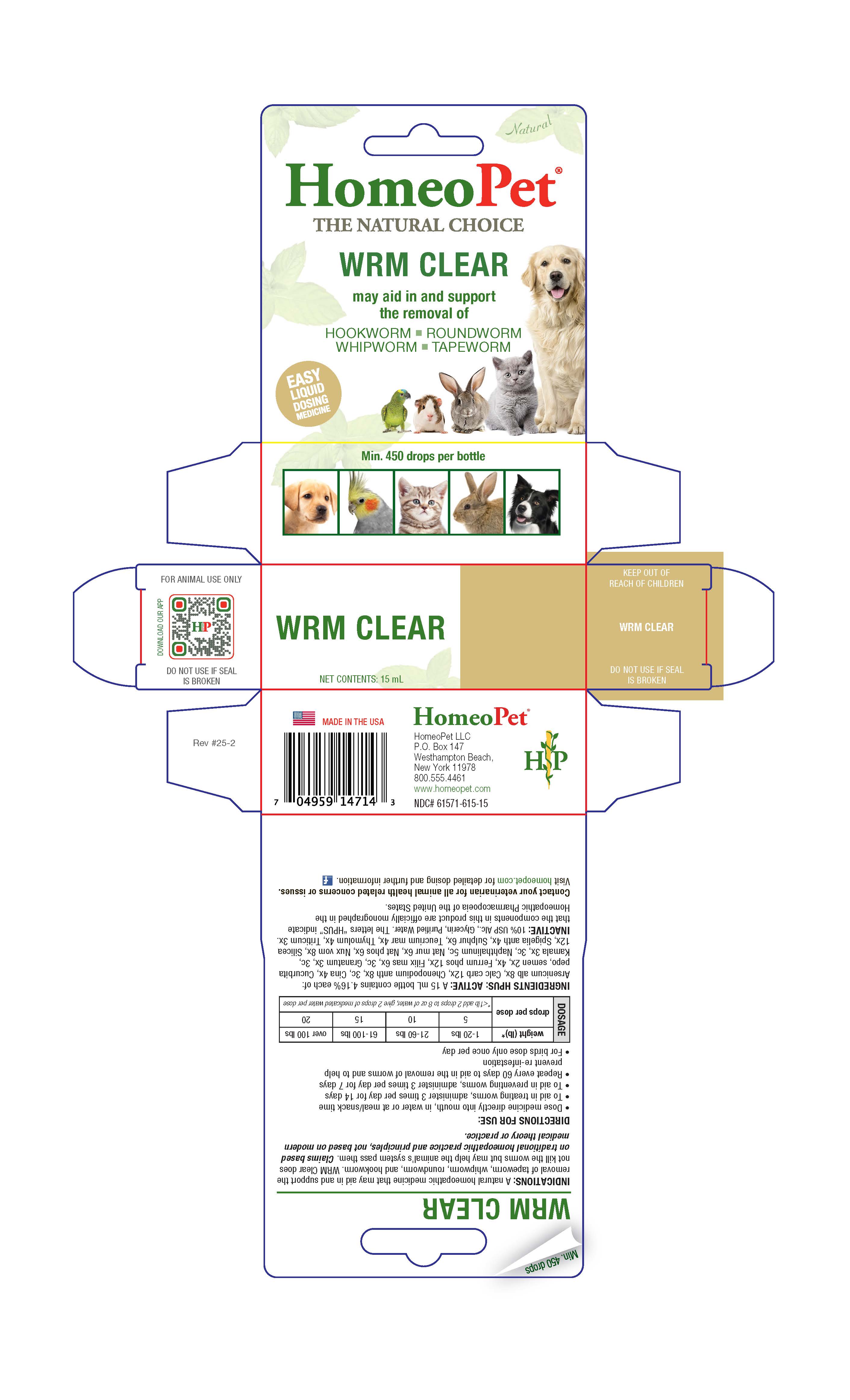 DRUG LABEL: Wrm Clear
NDC: 61571-615 | Form: LIQUID
Manufacturer: HomeoPet, LLC
Category: homeopathic | Type: OTC ANIMAL DRUG LABEL
Date: 20251216

ACTIVE INGREDIENTS: ARSENIC TRIOXIDE 8 [hp_X]/15 mL; OYSTER SHELL CALCIUM CARBONATE, CRUDE 12 [hp_X]/15 mL; CHENOPODIUM AMBROSIOIDES  8 [hp_X]/15 mL; ARTEMISIA CINA FLOWER 4 [hp_X]/15 mL; PUMPKIN SEED 2 [hp_X]/15 mL; FERRUM PHOSPHORICUM 12 [hp_X]/15 mL; DRYOPTERIS FILIX-MAS ROOT 6 [hp_X]/15 mL; PUNICA GRANATUM ROOT BARK 3 [hp_X]/15 mL; KAMALA 3 [hp_X]/15 mL; SODIUM PHOSPHATE, DIBASIC, HEPTAHYDRATE 6 [hp_X]/15 mL; NAPHTHALENE 5 [hp_C]/15 mL; STRYCHNOS NUX-VOMICA SEED 8 [hp_X]/15 mL; SILICON DIOXIDE 12 [hp_X]/15 mL; SPIGELIA ANTHELMIA 4 [hp_X]/15 mL; SULFUR 6 [hp_X]/15 mL; TEUCRIUM MARUM 4 [hp_X]/15 mL; THYMOL  4 [hp_X]/15 mL; ELYMUS REPENS TOP 3 [hp_X]/15 mL; SODIUM CHLORIDE 6 [hp_X]/15 mL
INACTIVE INGREDIENTS: ALCOHOL; WATER; GLYCERIN

WRM CLEAR

WRM Clear

May aid in and support the removal of

HOOKWORM-ROUNDWORM

WHIPWORM-TAPEWORM

Directions for Use and Dosage

- Dose remedy directly into mouth, in water or at meal/snack time
- To aid in treating worms, administer 3 times per day for 14 days
- To aid in preventing worms, administer 3 times per day for 7 days
- Repeat every 60 days to aid the removal of worms and to help prevent re-infestation
- For birds dose only once per day

DOSAGE | weight (lb)* | 1-20 lbs | 21-60 lbs | 61-100 lbs | over 100 lbs
DOSAGE | drops per dose | 5 | 10 | 15 | 20
DOSAGE | drops per dose | *<1 lb add 2 drops to 8 oz of water, give 2 drops of medicated water per dose

Contact Veterinary

Contact your veterinarian for all animal health related concerns or issues.

Visit homeopet.com for detailed dosing and further information.

Ingredients HPUS: Active

Arsenicum alb 8x, Calc carb 12x, Chenopodium anth 8x, 3c, Cina 4x, Cucurbita pepo, semen 2x, 4x, Ferrum phos 12x, Filix mas 6x, 3c, Granatum 3x, 3c, Kamala 3x, 3c, Naphthalinum 5c, Nat mur 6x, Nat phos 6x, Nux vom 8x, Silicea 12x, Spigelia anth 4x, Sulphur 6x, Teucrium mar 4x, Thymolum 4x, Triticum 3x.

Inactive Ingredients

USP Alcohol, Glyercin, Purified Water

INDICATIONS:

A natural homeopathic medicine that may aid in and support the removal of tapeworm, whipworm, roundworm and hookworm. WRM Clear does not kill the worms but can help the animals' system pass them. Claims based on traditional homeopathic practice and principles, not based on modern medical theory or practice.